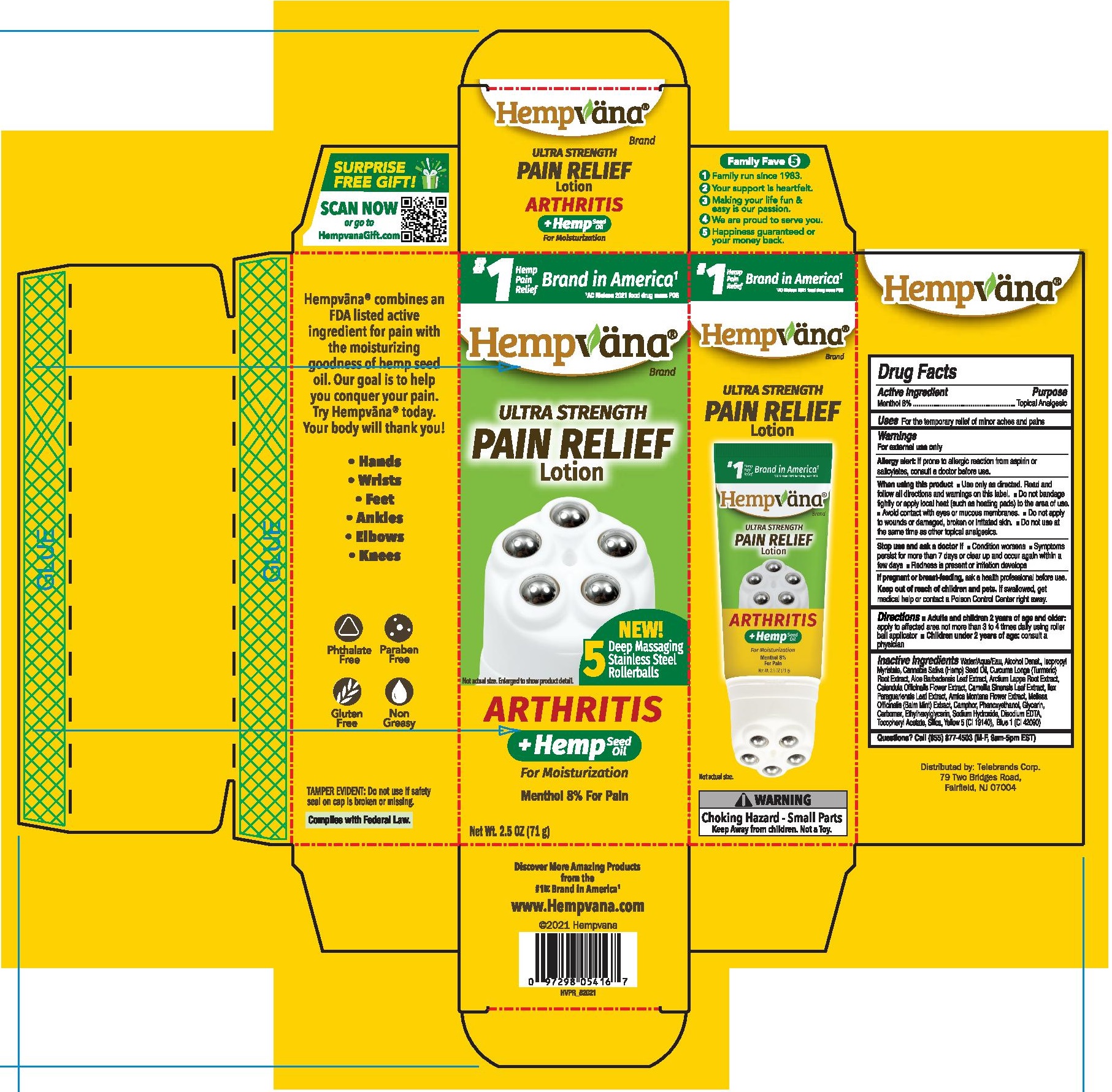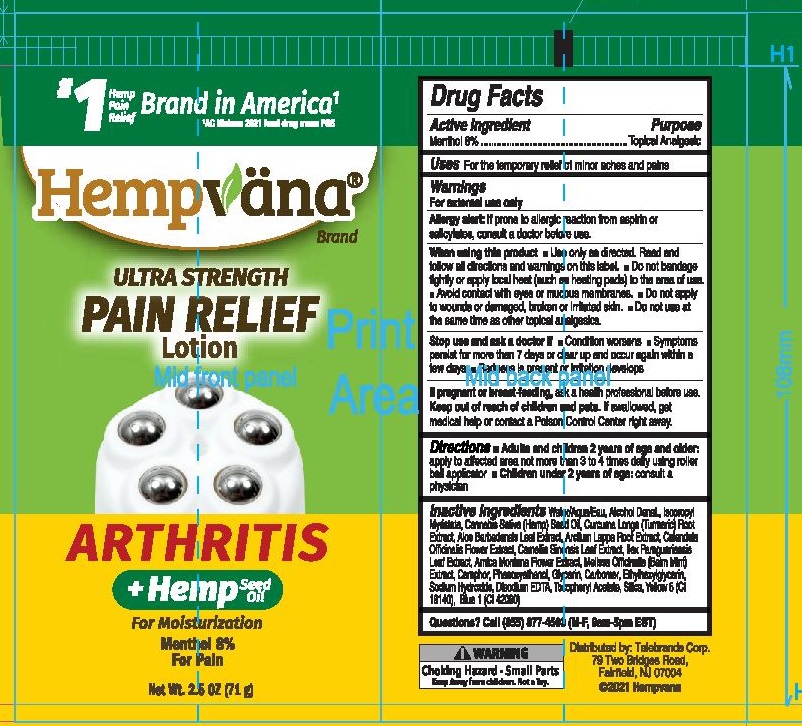 DRUG LABEL: Ultra Strength Pain Relief Gel
NDC: 73287-023 | Form: LOTION
Manufacturer: TELEBRANDS CORP
Category: otc | Type: HUMAN OTC DRUG LABEL
Date: 20241120

ACTIVE INGREDIENTS: MENTHOL 8 g/100 g
INACTIVE INGREDIENTS: ARNICA MONTANA FLOWER; CAMPHOR (NATURAL); ALCOHOL; WATER; PHENOXYETHANOL; GLYCERIN; CARBOMER HOMOPOLYMER, UNSPECIFIED TYPE; EDETATE DISODIUM ANHYDROUS; SILICON DIOXIDE; SODIUM HYDROXIDE; ETHYLHEXYLGLYCERIN; .ALPHA.-TOCOPHEROL ACETATE; FD&C YELLOW NO. 5; FD&C BLUE NO. 1; ISOPROPYL MYRISTATE; CANNABIS SATIVA SEED OIL; ALOE VERA LEAF; ARCTIUM LAPPA ROOT; GREEN TEA LEAF; MELISSA OFFICINALIS; TURMERIC; CALENDULA OFFICINALIS FLOWER; ILEX PARAGUARIENSIS LEAF

Hempvana Rollerballs (Arthritis)

Active Ingredient

Menthol 8%

Purpose

Menthol 8%....................Topical Analgesic

Uses

For the temporary relief of pain

Warnings

For external use only

Allergy alert:If prone to allergic reaction from aspirin or salicylates, consult a doctor before use.

When using this product

- Use only as directed. Read and follow all directions and warnings on this label.
- Do not bandage tightly or apply local heat (such as heating pads) to the area of use.
- Avoid contact with eyes or mucous membranes.
- Do not apply to wounds or damaged, broken or irritated skin.
- Do not use at the same time as other topical analgesics.

Stop use and ask a doctor if

- Condition worsens
- Symptoms persist for more than 7 days or clear up and occur again within a few days
- Redness is present or irritation develops

PREGNANCY OR BREAST FEEDING

If pregnant or breast-feeding,ask a health professional before use.

Keep out of reach of children and pets.If swallowed, get medical help or contact a Poison Control Center right away.

Directions

- Adults and children 2 years of age and older:apply to affected area not more than 3 to 4 times daily using roller ball applicator
- Children under 2 years of age:consult a physician

Inactive Ingredients

Water/Aqua/Eau, Alcohol Denat., Isopropyl Myristate, Cannabis Sativa (Hemp) Seed Oil, Curcuma Longa (Turmeric) Root Extract, Aloe Barbadensis Leaf Extract, Arctium Lappa Root Extract, Calendula Officinalis Flower Extract, Camellia Sinensis Leaf Extract, Ilex Paraguariensis Leaf Extract, Arnica Montana Flower Extract,, Melissa Officinalis (Balm Mint) Extract, Camphor, Phenoxyethanol, Glycerin, Carbomer, Ethylhexylglycerin, Sodium Hydroxide, Disodium EDTA, Tocopheryl Acetate, Silica, Yellow 5 (CI 19140), Blue 1 (CI 42090)

Questions?

Call (855) 877-4503 (M-F, 9am-5pm EST)

PACKAGE LABEL

#1 Hemp Pain Relief Brand in America^1

^1AC Nielsen 2021 food drug mass POS

Hempvana Brand

Ultra Strength Pain Relief Lotion

NEW! 5 Deep Massaging Stainless Steel Rollerballs

Arthritis

+ Hemp Seed Oil For Moisturization

Menthol 8% For Pain

Net Wt. 2.5 OZ (71g)